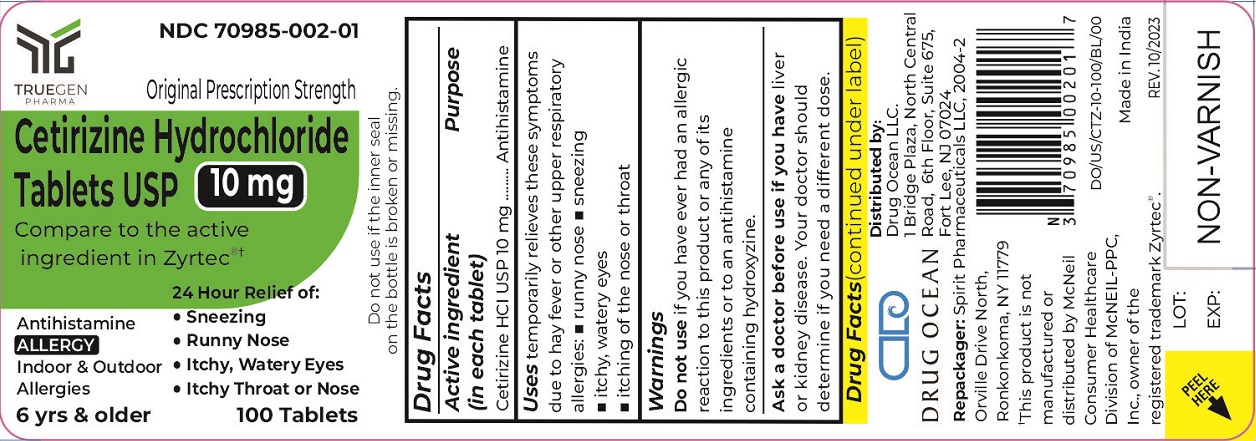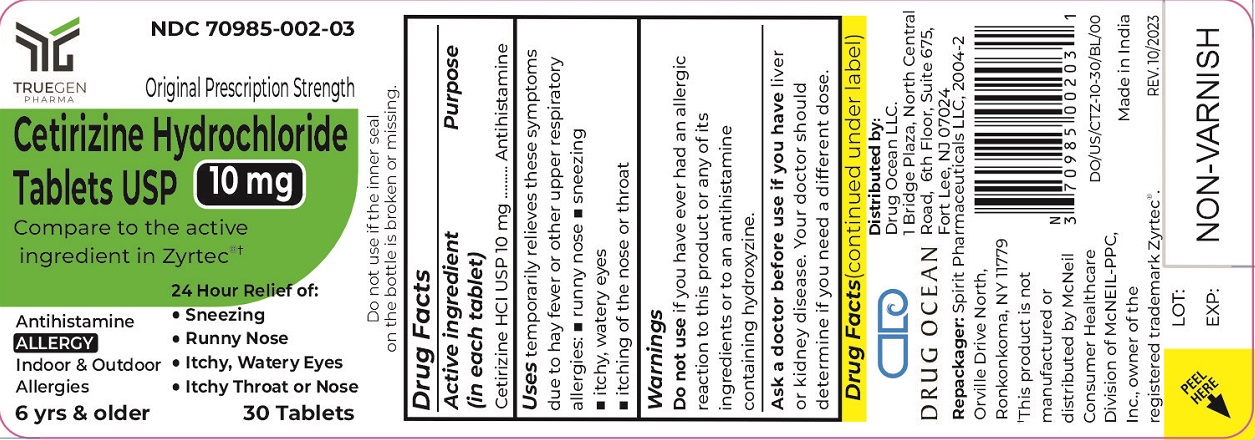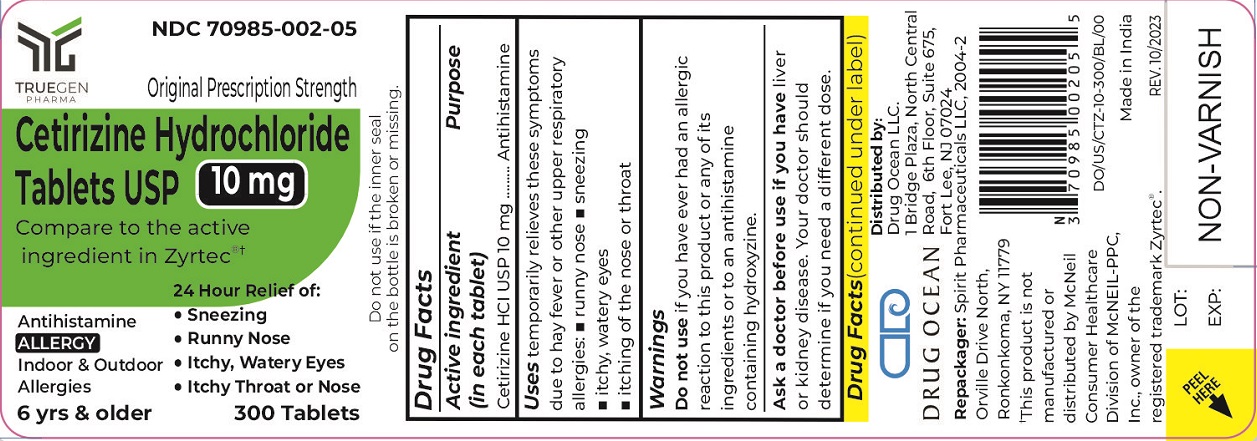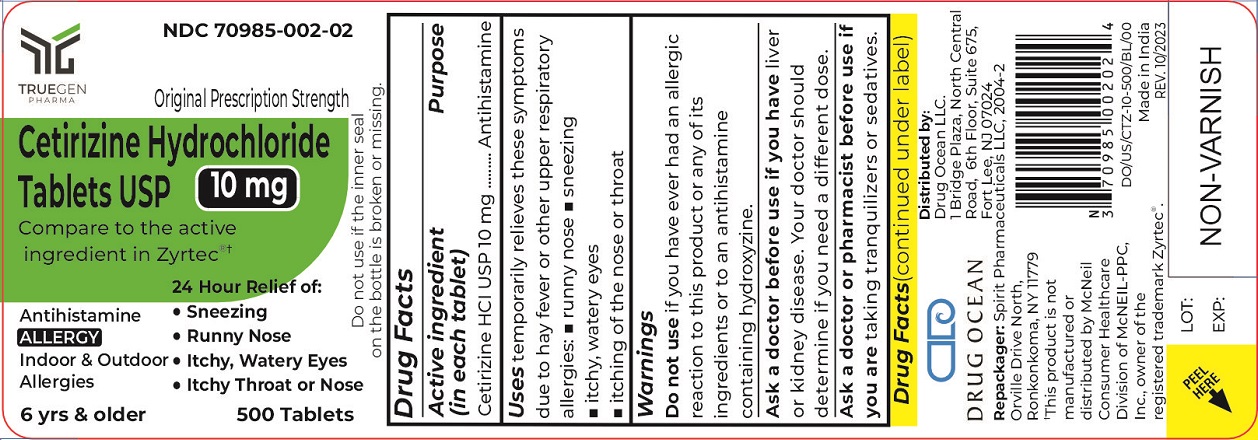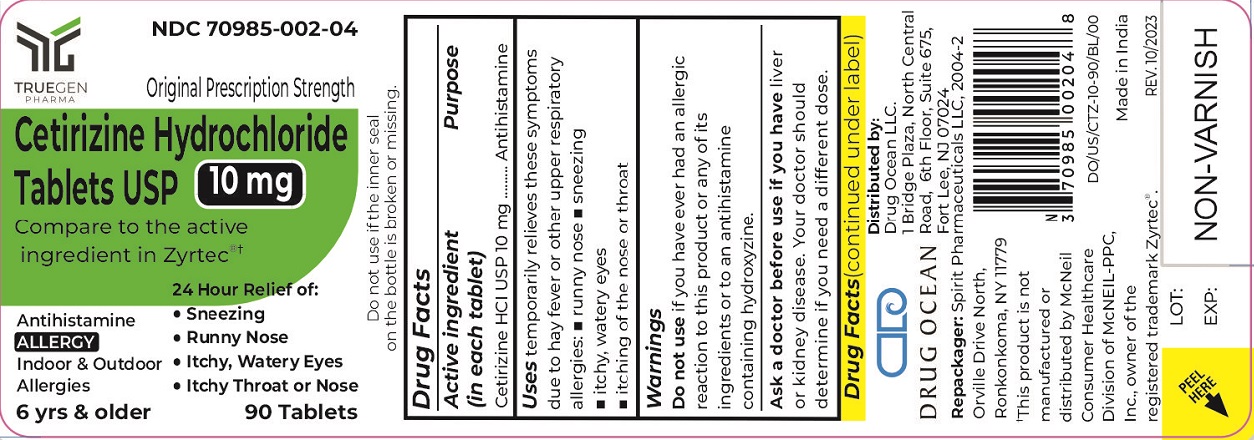 DRUG LABEL: Cetirizine Hydrochloride
NDC: 70985-002 | Form: TABLET
Manufacturer: Drug Ocean LLC
Category: otc | Type: HUMAN OTC DRUG LABEL
Date: 20231222

ACTIVE INGREDIENTS: CETIRIZINE HYDROCHLORIDE 10 mg/1 1
INACTIVE INGREDIENTS: LACTOSE; MAGNESIUM STEARATE; STARCH, CORN; POLYETHYLENE GLYCOL, UNSPECIFIED; POVIDONE; TITANIUM DIOXIDE; HYPROMELLOSES

Cetirizine Hydrochloride Tablets USP 10 mg
Drug Facts

Active Ingredients

Active Ingredient (in each tablet) Purpose
Cetirizine HCl USP 10 mg..............................................................................................Antihistimine

PURPOSE

Uses

Temporarily relieves these symptoms due to hay fever or other upper respiratory allergies

- runny nose
- sneezing
- itchy, watery eyes
- itching of the nose or throat

Warnings

Do Not Use if you have ever had an allergic reaction to this product or any of its ingredients or to an antihistamine containing hydroxyzine.

Ask a doctor before use if you have liver or kidney disease. Your doctor should determine if you need a different dose.

Ask a doctor or pharmacist before use if you are taking tranquilizers or sedatives.

When using this product

- drowsines may occur
- avoid alcoholic drinks
- alcohol, sedatives, and tranquilizers may increase drowsiness
- be careful when driving a motor vehicle or operating machinary.

Stop use and ask a doctor if an allergic reaction to this product occurs. Seek medical help right away.

If pregnant or breast-feeding:

- if breast-feeding: not recommended
- if pregnant: ask a health professional before use.

Keep out of reach of children.

In case of overdose, get medical help or contact Poison Control Center right away. (1-800-222-1222)

Directions

Adults and children 6 years and over | one 10 mg tablet once daily, do not take more than one 10 mg tablet in 24 hours. A 5 mg product may be appropriate for less sever symptoms.
Adults 65 years and over | Ask a doctor
Children under 6 years of age | Ask a doctor
Consumers with liver or kidney disease | Ask a doctor

Other Information

store between 20° to 25°C (68° to 77°F) [See USP Controlled Room Temperature]

Inactive Ingredients

Hypromellose, lactose, magnesium stearate, maize starch, polyethylene glycol, povidone, titanium dioxide.

Questions?

Call 1-866-333-9792

PACKAGE LABEL

DRUG OCEAN NDC 70985-002-01

Original Prescription Strength

Cetirizine Hydrochloride
Tablets USP

10 mg

6 yrs& older

100 Tablets

DRUG OCEAN NDC 70985-002-02

Original Prescription Strength

Cetirizine Hydrochloride
Tablets USP

10 mg

6 yrs& older

500 Tablets

DRUG OCEAN NDC 70985-002-03

Original Prescription Strength

Cetirizine Hydrochloride
Tablets USP

10 mg

6 yrs& older

30 Tablets

DRUG OCEAN NDC 70985-002-04

Original Prescription Strength

Cetirizine Hydrochloride
Tablets USP

10 mg

6 yrs& older

90 Tablets

DRUG OCEAN NDC 70985-002-05

Original Prescription Strength

Cetirizine Hydrochloride
Tablets USP

10 mg

6 yrs& older

300 Tablets